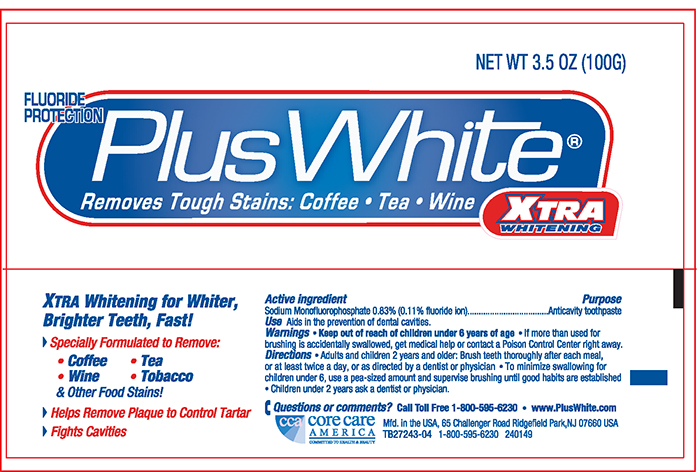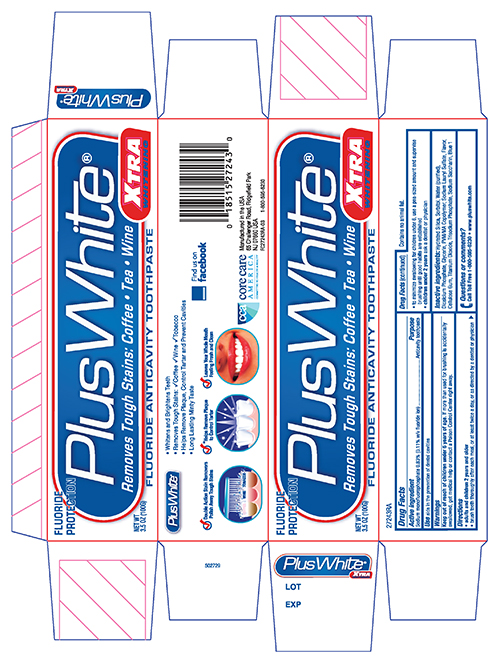 DRUG LABEL: Plus White Extra Whitening
NDC: 61543-1502 | Form: PASTE, DENTIFRICE
Manufacturer: CCA Industries LLC
Category: otc | Type: HUMAN OTC DRUG LABEL
Date: 20191226

ACTIVE INGREDIENTS: SODIUM MONOFLUOROPHOSPHATE 0.83 g/100 g
INACTIVE INGREDIENTS: GLYCERIN; WATER; HYDRATED SILICA; COPOVIDONE K25-31; TRIBASIC SODIUM PHOSPHATE; SODIUM LAURYL SULFATE; CARBOXYMETHYLCELLULOSE SODIUM; TITANIUM DIOXIDE; SACCHARIN SODIUM; SORBITOL; ANHYDROUS DIBASIC CALCIUM PHOSPHATE

Plus White Extra Whitening Toothpaste

Active ingredient

Sodium Monofluorophosphate 0.83% (0.15% w/v fluoride ion)

Purpose

Anticavity whitening toothpaste

Use

Aids in the removal of stains and prevention of dental decay.

Warnings

If more than used for brushing is accidentallly swallowed, get medical help or contact a Poison Control Center right away.

Keep out of reach of children under 6 years of age.

Directions

- adults and children 2 years and older
- Brush teeth thoroughly, after each meal, or at least twice a day, or as directed by a dentist or physician
- to minimize swallowing for children under the age of 6, use a pea size amountandsupervisebrushinguntil good habitsare established
- children under 2 years of ask a dentistor physician

INACTIVE INGREDIENT

Inactive ingredients Hydrated Silica, Sorbitol, Water (Aqua), Dicalcium Phosphate, Glycerin, PVM/MA Copolymer, Sodium Lauryl Sulfate, Flavor, Cellulose Gum, Titanium Dioxide, Trisodium Phosphate, Sodium Saccharin, Blue 1

Questions or comments? Call Toll Free1-800-595-6230
- www.pluswhite.com

Plus White Extra Whitening -Carton 3.5 oz

Plus+White Extra Whitening

Fluoride Protection

Fluoride Anticavity toothpaste

NET WT. 3.5 oz (100G)

Plus White Extra Whitening -Tube 3.5 oz

Plus +White Extra Whitening

Fluoride Protection

NET WT 3.5 oz (100G)